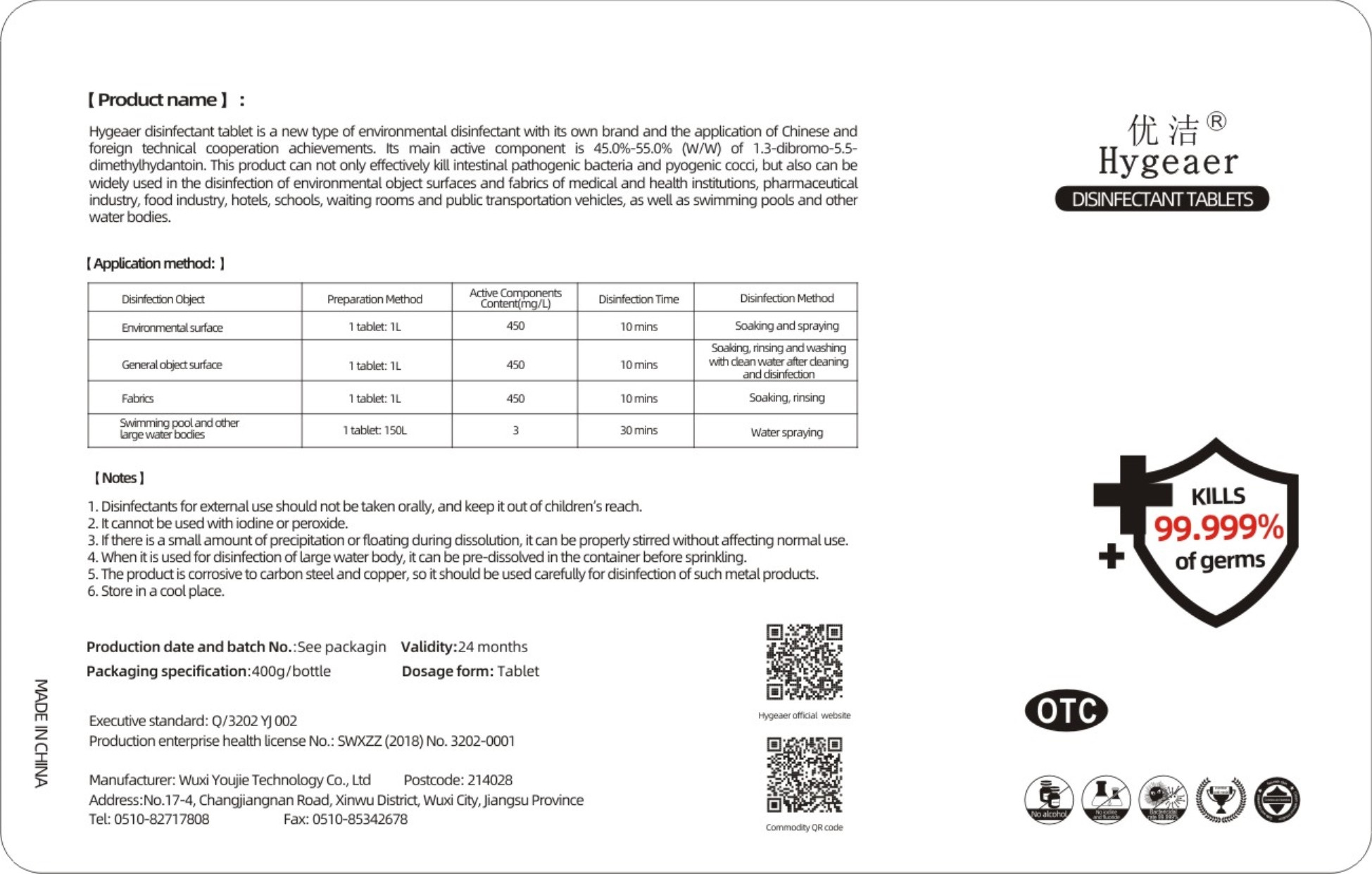 DRUG LABEL: DisinfectantTablets
NDC: 54796-004 | Form: GRANULE
Manufacturer: Wuxi Youjie Technology Co. LTD
Category: otc | Type: HUMAN OTC DRUG LABEL
Date: 20200428

ACTIVE INGREDIENTS: 1,3-DIBROMO-5,5-DIMETHYLHYDANTOIN 200 g/400 g
INACTIVE INGREDIENTS: SODIUM CHLORIDE; SODIUM SULFATE

DOSAGE AND ADMINISTRATION

Store in a cool place.

INACTIVE INGREDIENT

SODIUM SULFATE
SODIUM CHLORIDE

INDICATIONS AND USAGE

Enmironmental suface: 1 tablet: 1L 450mg/L 10 mins Soaking and spraying.

General object surface: 1 tablet: 1L 450mg/L 10mins Soaking, rinsing andwashing with dean water after cleaning and disinfedion.

Fabrics: 1 tablet: 1L 450mg/L 10 mins Soaking, rinsing.

Swimming pool and other large water bodies: 1 tablet: 1L 3mg/L 10 mins water spraying.

ACTIVE INGREDIENT

1,3-DIBROMO-5,5-DIMETHYLHYDANTOIN

keep out of reach of children

PURPOSE

Disinfection
Sterilization

WARNINGS

1. Disinfectants for extemal use should not be taken orally, and keep it out of children's reach.
2. It cannot be used with iodine or peroxide.
3. If there is a small amount of precipitation or floating during dissolution, itcan be properly strred without affecting normaluse.
4. When itis used for disinfection of large water body, it can be pre-dissolved in the container before sprinkling.
5. The product is corrosive to carbon steel and copper, so it should be used carefully for disinfection of such metal products.
6. Store in a cool place.